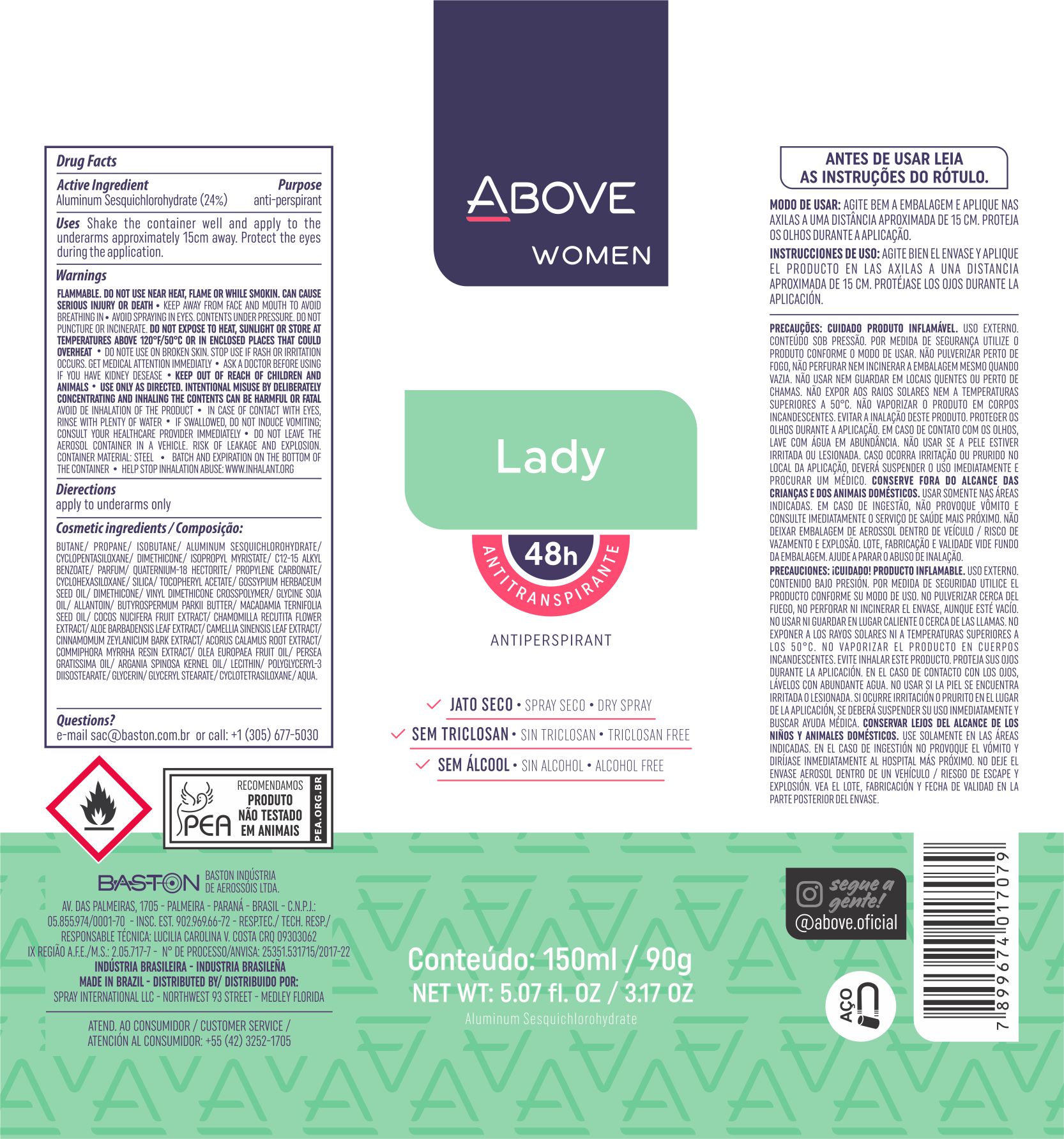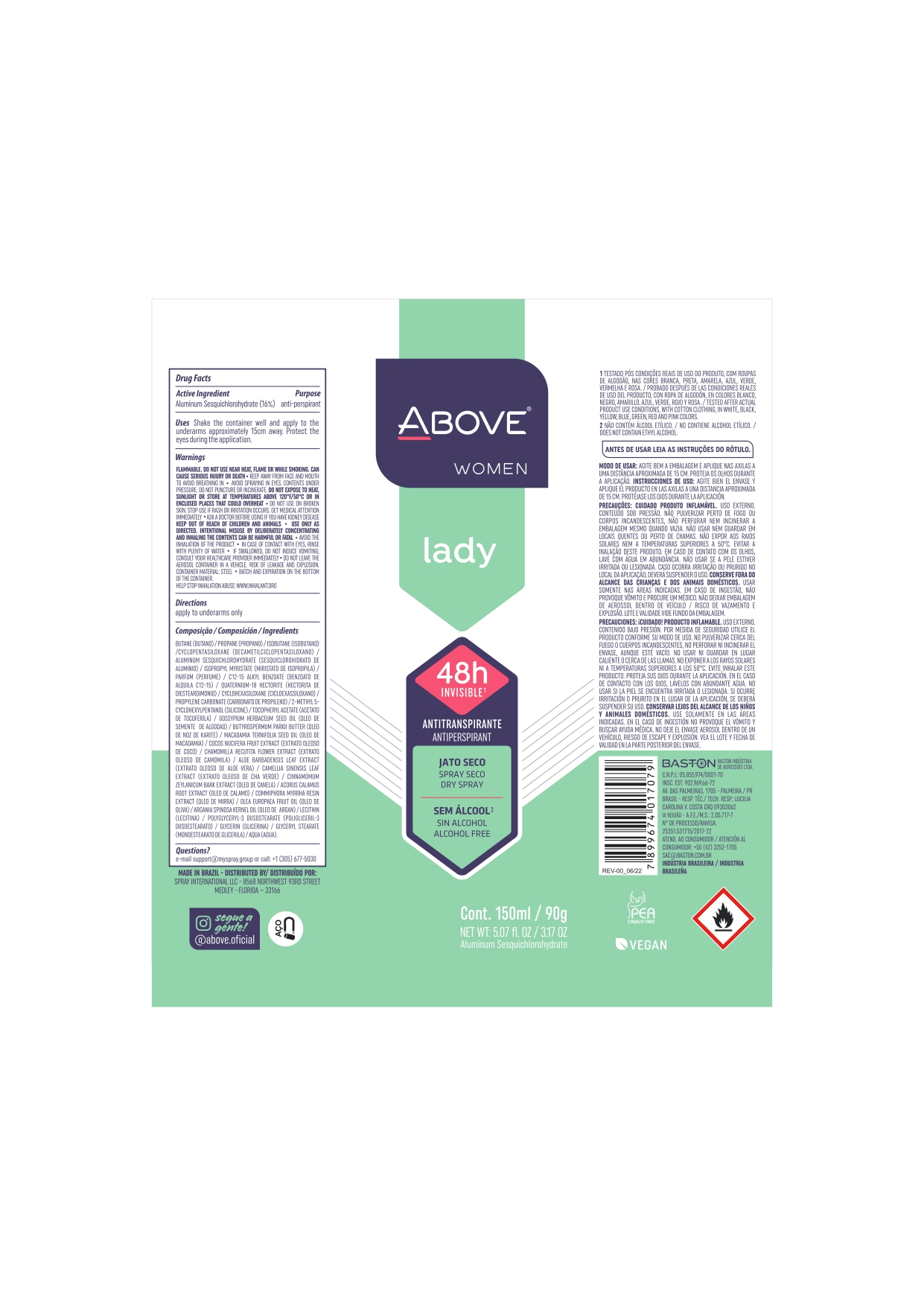 DRUG LABEL: Antiperspirant Above Lady
NDC: 73306-1104 | Form: AEROSOL, SPRAY
Manufacturer: Baston Industria de Aerossóis Ltda
Category: otc | Type: HUMAN OTC DRUG LABEL
Date: 20241009

ACTIVE INGREDIENTS: ALUMINUM SESQUICHLOROHYDRATE 24 g/100 g
INACTIVE INGREDIENTS: CYCLOMETHICONE 5; GLYCERIN; VINYL DIMETHICONE/METHICONE SILSESQUIOXANE CROSSPOLYMER; SHEA BUTTER; SILICA DIMETHYL SILYLATE; ALLANTOIN; LECITHIN, SOYBEAN; .ALPHA.-TOCOPHEROL ACETATE; POLYGLYCERYL-3 DIISOSTEARATE; ARGAN OIL; MYRRH OIL; BUTANE; AVOCADO OIL; CINNAMON BARK OIL; PROPYLENE CARBONATE; ALOE VERA LEAF; GLYCERYL MONOSTEARATE; GREEN TEA LEAF; WATER; ISOPROPYL MYRISTATE; COCONUT; ACORUS CALAMUS ROOT; CHAMOMILE; ISOBUTANE; PROPANE; DISTEARDIMONIUM HECTORITE; DIMETHICONE; LEVANT COTTON SEED; MACADAMIA OIL

Antiperspirant Above Lady